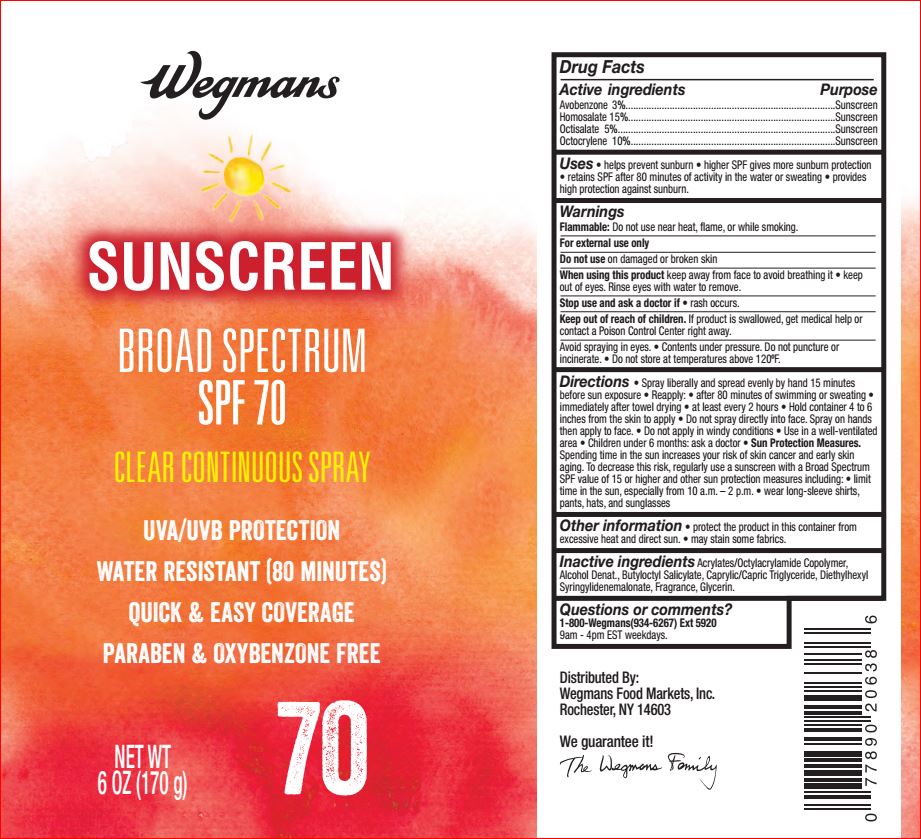 DRUG LABEL: Sunscreen SPF 70
NDC: 47124-115 | Form: SPRAY
Manufacturer: Wegman
Category: otc | Type: HUMAN OTC DRUG LABEL
Date: 20180705

ACTIVE INGREDIENTS: Avobenzone 3 g/100 g; Homosalate 15 g/100 g; Octisalate 5 g/100 g; Octocrylene 10 g/100 g
INACTIVE INGREDIENTS: ALCOHOL; Butyloctyl Salicylate; MEDIUM-CHAIN TRIGLYCERIDES; Diethylhexyl Syringylidenemalonate; Glycerin

Drug Facts

Active ingredients Purpose
Avobenzone 3%.................................................................................Sunscreen
Homosalate 15%................................................................................Sunscreen
Octisalate 5%....................................................................................Sunscreen
Octocrylene 10%...............................................................................Sunscreen

INDICATIONS AND USAGE

Uses • helps prevent sunburn • higher SPF gives more sunburn protection
• retains SPF after 80 minutes of activity in the water or sweating • provides
high protection against sunburn

Warnings
Flammable: Do not use near heat, flame, or while smoking.
For external use only
Do not use on damaged or broken skin
When using this product keep away from face to avoid breathing it • keep
out of eyes. Rinse eyes with water to remove.
Stop use and ask a doctor if • rash occurs.
Keep out of reach of children. If product is swallowed, get medical help or
contact a Poison Control Center right away.
Avoid spraying in eyes. • Contents under pressure. Do not puncture or
incinerate. • Do not store at temperatures above 120ºF

DOSAGE AND ADMINISTRATION

Directions • Spray liberally and spread evenly by hand 15 minutes
before sun exposure • Reapply: • after 80 minutes of swimming or sweating •
immediately after towel drying • at least every 2 hours • Hold container 4 to 6
inches from the skin to apply • Do not spray directly into face. Spray on hands
then apply to face. • Do not apply in windy conditions • Use in a well-ventilated
area • Children under 6 months: ask a doctor • Sun Protection Measures.
Spending time in the sun increases your risk of skin cancer and early skin
aging. To decrease this risk, regularly use a sunscreen with a Broad Spectrum
SPF value of 15 or higher and other sun protection measures including: • limit
time in the sun, especially from 10 a.m. – 2 p.m. • wear long-sleeve shirts,
pants, hats, and sunglasses

Other information • protect the product in this container from
excessive heat and direct sun. • may stain some fabrics.

Inactive ingredients

Acrylates/Octylacrylamide Copolymer,
Alcohol Denat., Butyloctyl Salicylate, Caprylic/Capric Triglyceride, Diethylhexyl
Syringylidenemalonate, Fragrance, Glycerin

Questions or comments?
1-800-Wegmans(934-6267) Ext 5920
9am - 4pm EST weekdays.